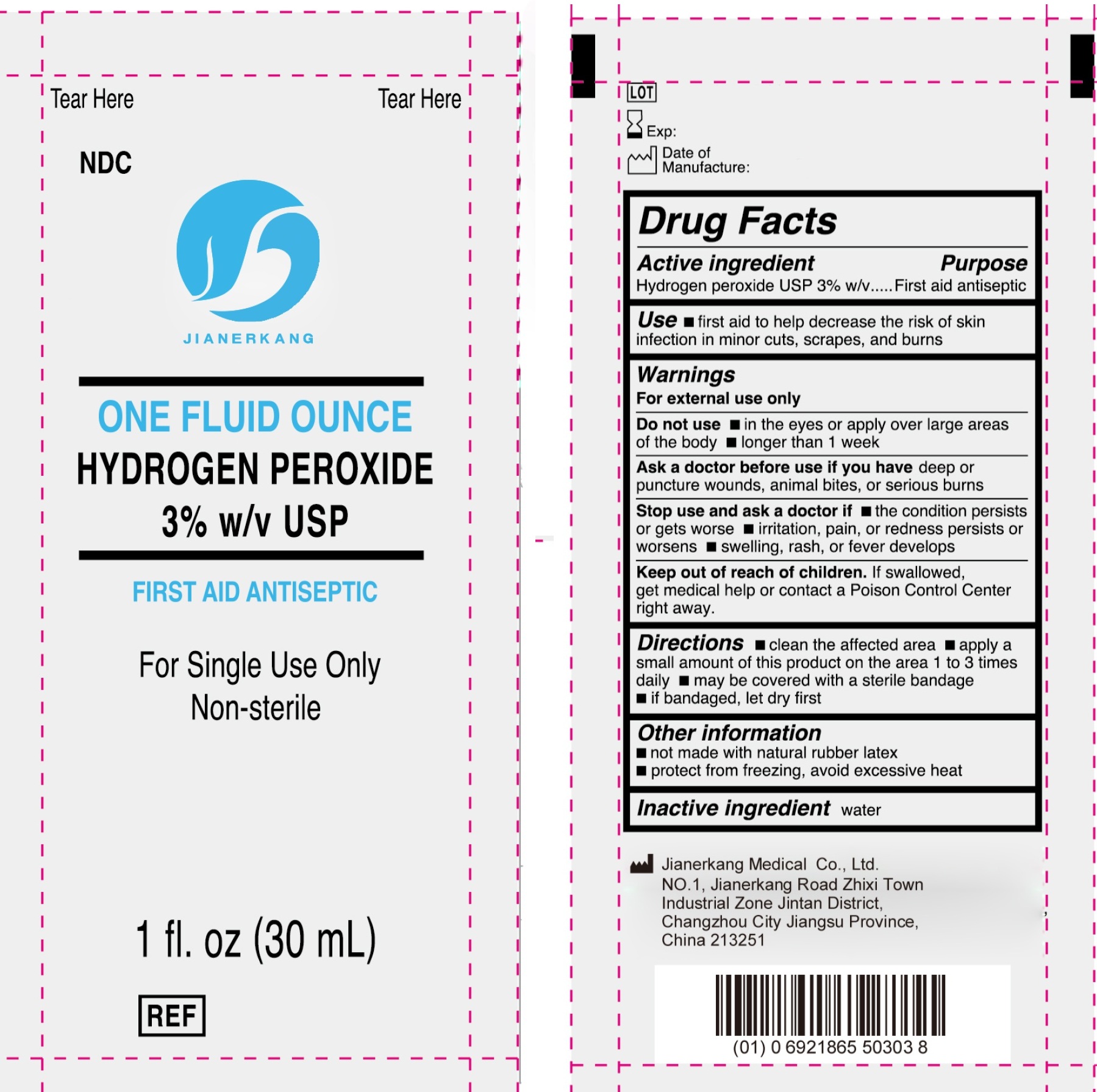 DRUG LABEL: Hydrogen Peroxide
NDC: 34645-0027 | Form: SOLUTION
Manufacturer: Jianerkang Medical Co., Ltd
Category: otc | Type: HUMAN OTC DRUG LABEL
Date: 20250131

ACTIVE INGREDIENTS: HYDROGEN PEROXIDE 30 mg/1 mL
INACTIVE INGREDIENTS: WATER

Hydrogen Peroxide 3%

Active ingredient

Hydrogen peroxide USP 3% w/v

Purpose

First aid antiseptic

Use

- first aid to help decrease the risk of skin infection in minor cuts, scrapes, and burns

Warnings

For external use only

Do not use

- in the eyes or apply over large areas of the body
- longer than 1 week

Ask a doctor before use if you have

deep or puncture wounds, animal bites, or serious burns

Stop use and ask a doctor if

- the condition persists or gets worse
- irritation, pain, or redness persists or worsens
- swelling, rash, or fever develops

Keep out of reach of children.

If swallowed, get medical help or contact a Poison Control Center right away.

Directions

- clean the affected area
- apply a small amount of this product on the area 1 to 3 times daily
- may be covered with a sterile bandage
- if bandaged, let dry first

Other information

- not made with natural rubber latex
- protect from freezing, avoid excessive heat

Inactive ingredient

water